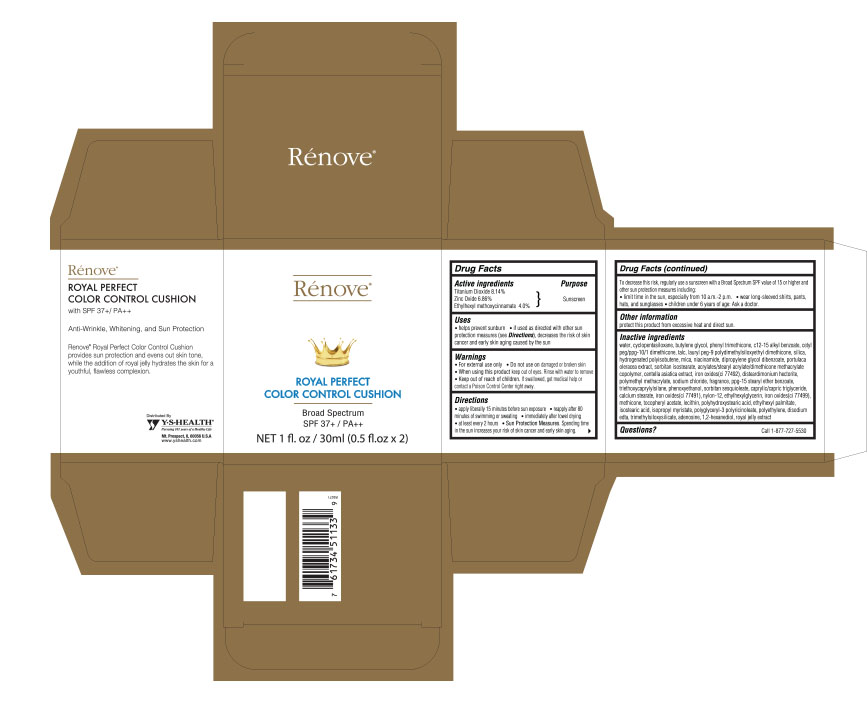 DRUG LABEL: Renove Royal Perfect Color Control Cushion SPF 37 / PA
NDC: 60782-002 | Form: CREAM
Manufacturer: Y.S. Health Corp.
Category: otc | Type: HUMAN OTC DRUG LABEL
Date: 20160118

ACTIVE INGREDIENTS: TITANIUM DIOXIDE 81.4 mg/1 mL; ZINC OXIDE 68.6 mg/1 mL; OCTINOXATE 40 mg/1 mL
INACTIVE INGREDIENTS: WATER; CYCLOMETHICONE 5; BUTYLENE GLYCOL; PHENYL TRIMETHICONE; C12-15 ALKYL BENZOATE; TALC; LAURYL PEG-9 POLYDIMETHYLSILOXYETHYL DIMETHICONE; SILICON DIOXIDE; MICA; NIACINAMIDE; DIPROPYLENE GLYCOL DIBENZOATE; PURSLANE; SORBITAN ISOSTEARATE; CENTELLA ASIATICA; FERRIC OXIDE RED; DISTEARDIMONIUM HECTORITE; SODIUM CHLORIDE; PPG-15 STEARYL ETHER BENZOATE; TRIETHOXYCAPRYLYLSILANE; PHENOXYETHANOL; SORBITAN SESQUIOLEATE; TRICAPRIN; CALCIUM STEARATE; NYLON-12; ETHYLHEXYLGLYCERIN; .ALPHA.-TOCOPHEROL ACETATE; ETHYLHEXYL PALMITATE; ISOSTEARIC ACID; ISOPROPYL MYRISTATE; HIGH DENSITY POLYETHYLENE; EDETATE DISODIUM; ADENOSINE; 1,2-HEXANEDIOL

Renove Royal Perfect Color Control Cushion SPF 37+ / PA++

ACTIVE INGREDIENTS

Titanium Dioxide 8.14%

Zinc Oxide 6.86%

Ethylhexyl methoxycinnamate 4.0%

PURPOSE

Sunscreen

USES

- helps prevent sunburn
- if used as directed with other sun protection measures (see Directions), decreases the risk of skin cancer and early skin aging caused by the sun

WARNINGS

- For external use only

Do not use on

damaged or broken skin

When using this product

keep out of eyes. Rinse with water to remove

Keep out of reach of children.

If swallowed, get medical help or contact a Poison Control Center right away.

DIRECTIONS

- Apply liberally 15 minutes before sun exposure.
- Reapply after 80 minutes of swimming or sweating.
- Immediately after towel drying
- At least every 2 hours
- Sun protection Measures. Spending time in the sun increases your risk of skin cancer and early skin aging. To decrease this risk, regularly use a sunscreen with a Broad Spectrum SPF value of 15 or higher and other sun protection measures including:

• Limit time in the sun, especially from 10 a.m.-2 p.m.

• Wear long-sleeved shirts, pants, hats, and sunglasses

- Children under 6 years of age: Ask a doctor.

INACTIVE INGREDIENTS

1. Water, Cyclopentasiloxane, Butylene Glycol, Ethylhexyl Methoxycinnamate, Phenyl Trimethicone, C12-15 Alkyl Benzoate, Cetyl PEG/PPg-10/1 Dimethicone, Talc, Lauryl PEG-9 Polydimethylsiloxyethyl Dimethicone, Silica, Hydrogenated Polyisobutene, Mica, Niacinamide, Dipropylene Glycol Dibenzoate, Portulaca Oleracea Extract, Sorbitan Isostearate, Acrylates/Stearyl Acrylate/Dimethicone Methacrylate Copolymer, Centella Asiatica Extract, Iron Oxides(CI 77492), Disteardimonium Hectorite, Polymethyl Methacrylate, Sodium Chloride, Fragrance, PPG-15 Stearyl Ether Benzoate, Triethoxycaprylylsilane, Phenoxyethanol, Sorbitan Sesquioleate, Caprylic/Capric Triglyceride, Calcium Stearate, Iron Oxides(CI 77491), Nylon-12, Ethylhexylglycerin, Iron Oxides(CI 77499), Methicone, Tocopheryl Acetate, Lecithin, Polyhydroxystearic Acid, Ethylhexyl Palmitate, Isostearic Acid, Isopropyl Myristate, Polyglyceryl-3 Polyricinoleate, Polyethylene, Disodium EDTA, Trimethylsiloxysilicate, Adenosine, 1,2-Hexanediol, Royal Jelly Extract

OTHER INFORMATION

Protect this product from excessive heat and direct sun.